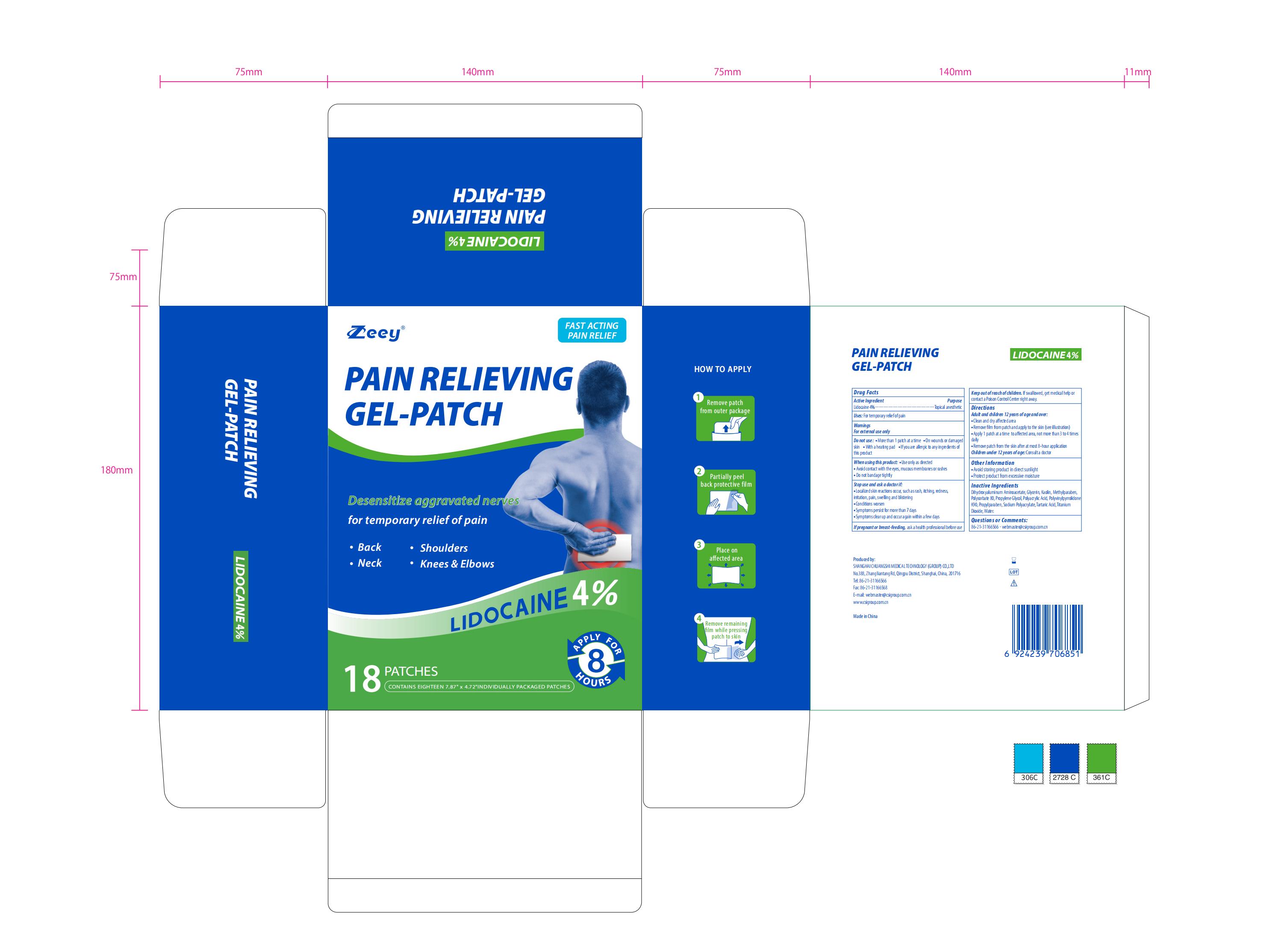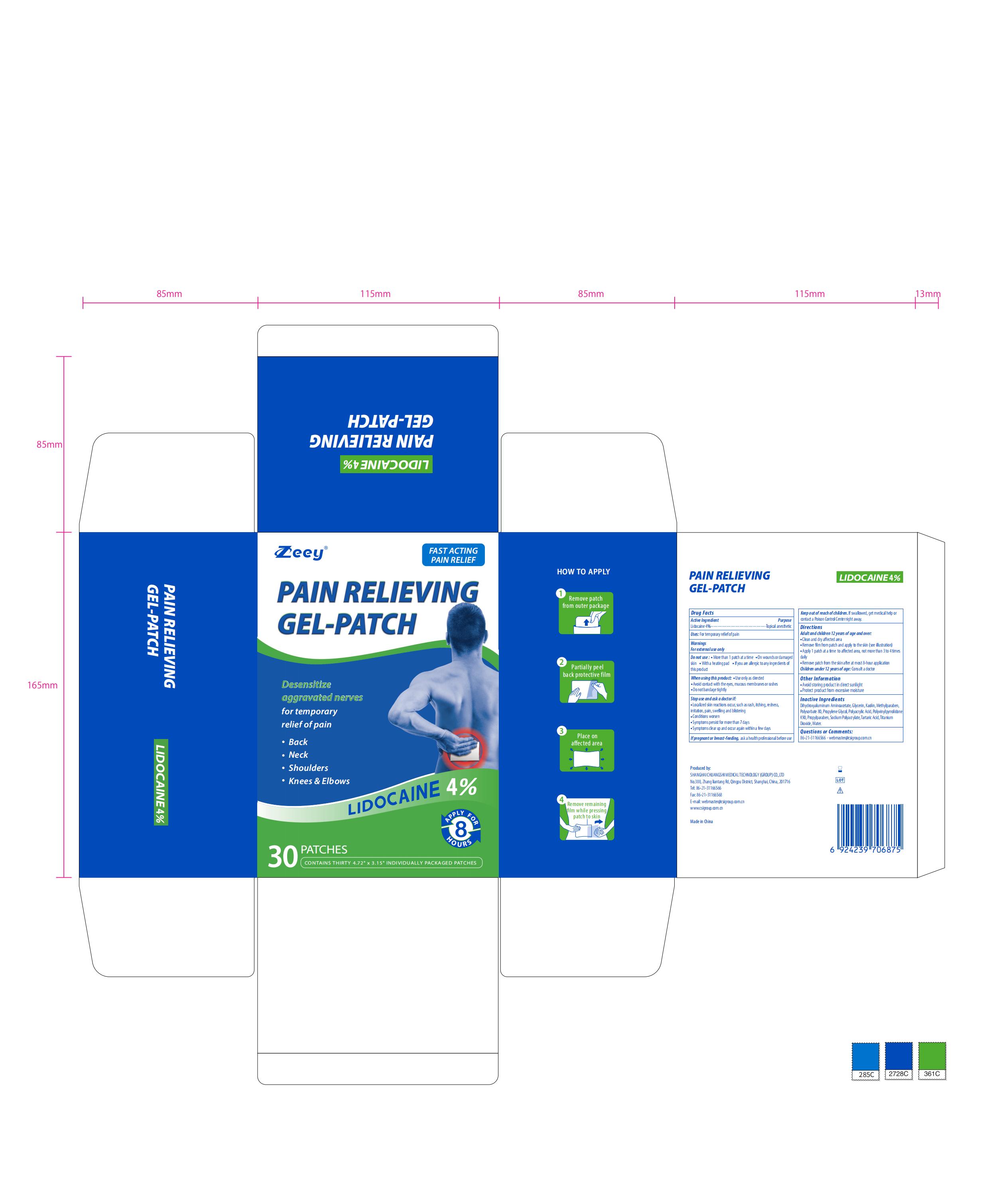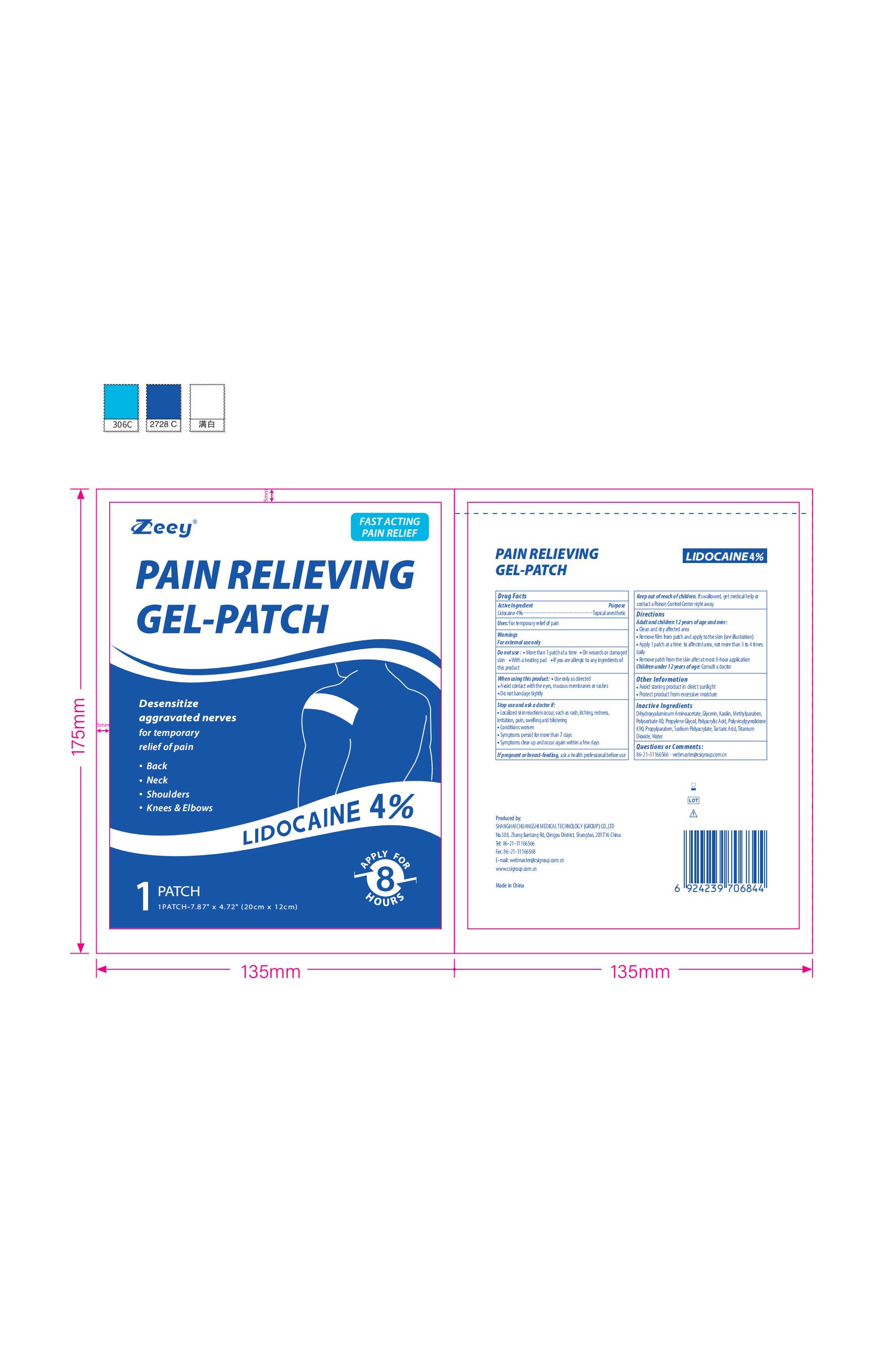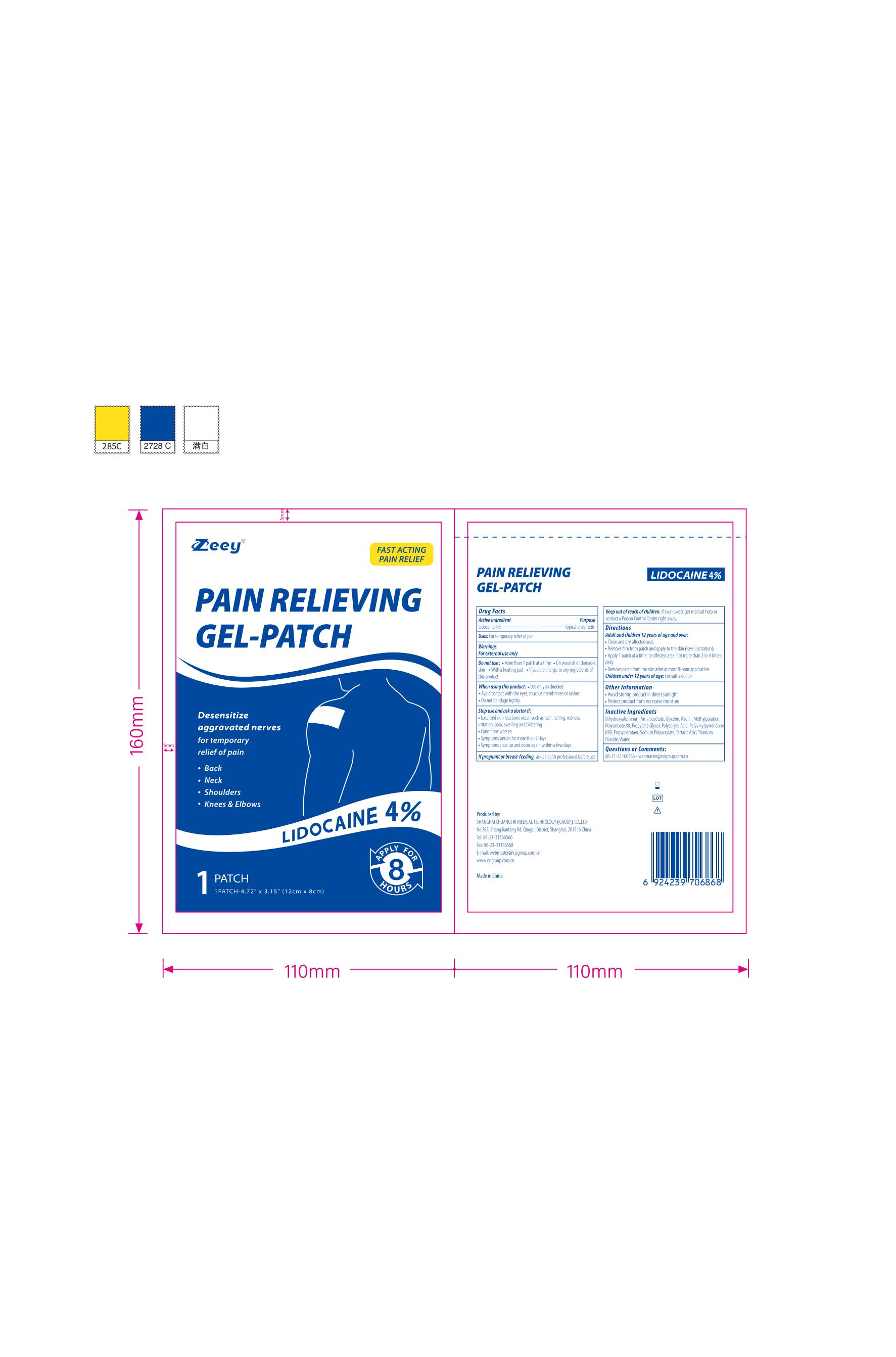 DRUG LABEL: Pain Relieving Gel-Patch
NDC: 73557-160 | Form: PATCH
Manufacturer: Shanghai Chuangshi Medical Technology (Group) Co., Ltd.
Category: otc | Type: HUMAN OTC DRUG LABEL
Date: 20250615

ACTIVE INGREDIENTS: LIDOCAINE 0.04 g/1 g
INACTIVE INGREDIENTS: POLYSORBATE 80; GLYCERIN; POVIDONE K90; METHYLPARABEN; PROPYLPARABEN; KAOLIN; TARTARIC ACID; WATER; PROPYLENE GLYCOL; POLYACRYLIC ACID (250000 MW); SODIUM POLYACRYLATE (2500000 MW); TITANIUM DIOXIDE; DIHYDROXYALUMINUM AMINOACETATE ANHYDROUS

CSI, Pain Relieving Gel-Patch, Lidocaine 4%, 18 Patches；30Patches

Active Ingredient

Lidocaine 4% ...... Purpose: Topical Anesthetic

Uses

For temporary relief of pain

Warnings

For external use only

Do not use

- More than 1 patch at a time
- On wounds or damaged skin
- With a heating pad
- If you are allergic to any ingredients of this product

When using this product

- Use only as directed
- Avoid contact with the eyes, mucous membranes or rashes
- Do not bandage tightly

Stop use ... if

- localized skin reactions occur, such as rash, itching, redness, irritation, pain, swelling and blistering
- Conditions worsen
- Symptoms persists for more than 7 days
- Symptoms clear up and occur again within a few days

... ask a doctor if

- localized skin reactions occur, such as rash, itching, redness, irritation, pain, swelling and blistering
- Conditions worsen
- Symptoms persists for more than 7 days
- Symptoms clear up and occur again within a few days

If pregnant or breast-feeding

ask a health professional before use

Keep out of reach of children

If swallowed, get medical help or contact a Poison Control Center right away.

Directions

Adult and Children 12 years of age and over:

- Clean and dry affected area
- Remove film from patch and apply to the skin (see illustration)
- Apply 1 patch at a time to affected area, not more than 3 to 4 times daily
- Remove patch from the skin after at most 8-hour application

Children under 12 years of age: Consult a doctor

Dosage forms & strengths

This is a strip, patch dosage form.

The active ingredient strength is 4% w/w.

One patch one time, no more than 8 hours one time.

Other information

- Avoid storing product in direct sunlight
- Protect product from excessive moisture

Inactive Ingredients

Dihydroxyaluminum Aminoacetate, Glycerin, Kaolin, Methylparaben, Polysorbate 80, Propylene Glycol, Polyacrylic Acid, Polyvinylpyrrolidone K90, Propylparaben, Sodium Polyacrylate, Tartaric Acid, Titanium Dioxide, Water

Questions or Comments

86-21-31166566

webmaster@csigroup.com.cn